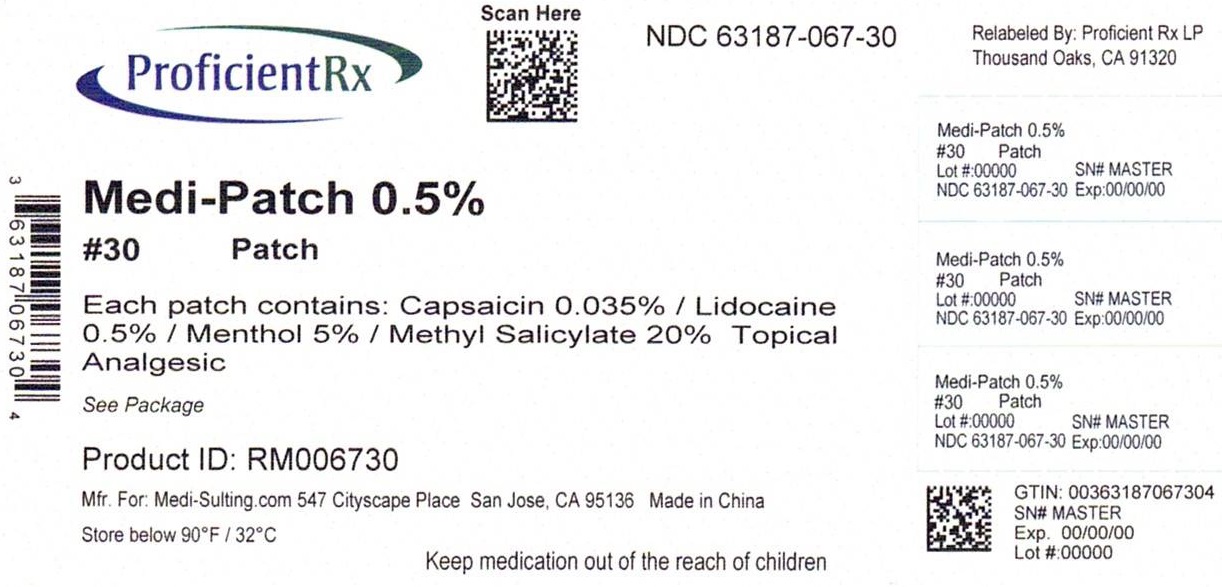 DRUG LABEL: MEDI-SULTING TOPICAL PAIN RELIEF
NDC: 63187-067 | Form: PATCH
Manufacturer: Proficient Rx LP
Category: otc | Type: HUMAN OTC DRUG LABEL
Date: 20240101

ACTIVE INGREDIENTS: METHYL SALICYLATE 20 g/100 g; MENTHOL, UNSPECIFIED FORM 5 g/100 g; CAPSAICIN .035 g/100 g; LIDOCAINE 0.5 g/100 g
INACTIVE INGREDIENTS: ACRYLIC ACID; ALUMINUM HYDROXIDE; CROSCARMELLOSE SODIUM; ETHYLHEXYL ACETATE; GLYCERIN; ISOPROPYL MYRISTATE; METHYL ACRYLATE; NONOXYNOL-30; SODIUM POLYACRYLATE (2500000 MW); POLYACRYLIC ACID (800000 MW); POLYSORBATE 80; SORBITAN SESQUIOLEATE; STARCH, CORN; TALC; TARTARIC ACID; TITANIUM DIOXIDE; WATER

ACTIVE INGREDIENT

CAPSAICIN 0.035%

LIDOCAINE 0.5%

MENTHOL 5%

METHYL SALICYLATE 20%

PURPOSE

TOPICAL ANALGESIC

TOPICAL ANESTHETIC

INDICATIONS AND USAGE

USES: FOR THE TEMPORARY RELIEF OF MINOR ACHES AND PAINS OF MUSCLES AND JOINTS ASSOCIATED WITH ARTHRITIS, SIMPLE BACKACHE, STRAINS, SPRAINS, MUSCLE SORENESS AND STIFFNESS.

DO NOT USE: ON WOUNDS OR DAMAGED SKIN. CHILDREN UNDER 12 YEARS OLD, CONSULT A DOCTOR. IF YOU ARE ALLERGIC TO ANY INGREDIENTS IN THIS PRODUCT.

DOSAGE AND ADMINISTRATION

Directions: Use only as directed. Prior to first use, test skin sensitivity by applying a small amount. Apply and massage directly to affected area. Do not use more than 4 times a day. Thoroughly wash hands after application.

INACTIVE INGREDIENT

Inactive Ingredients: ACRLIC ACID, ALUMINUM HYDROXIDE, CARMELLOSE SODIEM, 2-ETHYLHEXYL ACRYLATE, GLYCERIN, ISOPROPYL MYRISTATE, METHYL ACRYLATE, NONOXYNOL-30, POLYACRYLATE, POLYACRYLIC ACID, POLYSORBATE 80, SORBITAN SESQUIOLEATE, STARCH, TALC, TARTARIC ACID, TITANIUM DIOXIDE, WATER.

OTHER INFORMATION: STORE BELOW 90°F/32°C

QUESTIONS? 888 907-2833

ASK DOCTOR

IF CONDITION WORSENS, OR IF SYMPTOMS PERSIST FOR MORE THAN 7 DAYS OR CLEAR UP AND OCCUR AGAIN WITHIN A FEW DAYS, DISCONTINUE USE OF THIS PRODUCT AND CONSULT A DOCTOR.

IF PREGNANT OR NURSING ASK A HEALTH PROFESSIONAL BEFORE USE.

KEEP OUT OF REACH OF CHILDREN.

Warnings

Warnings: For external use only. Use only as directed. Avoid contact with eyes and mucous membranes. Do not use with heating devices or pads. Do not cover or bandage tightly. If swallowed, call poison control. If contact does occur with eyes rinse with cold water and call a doctor.